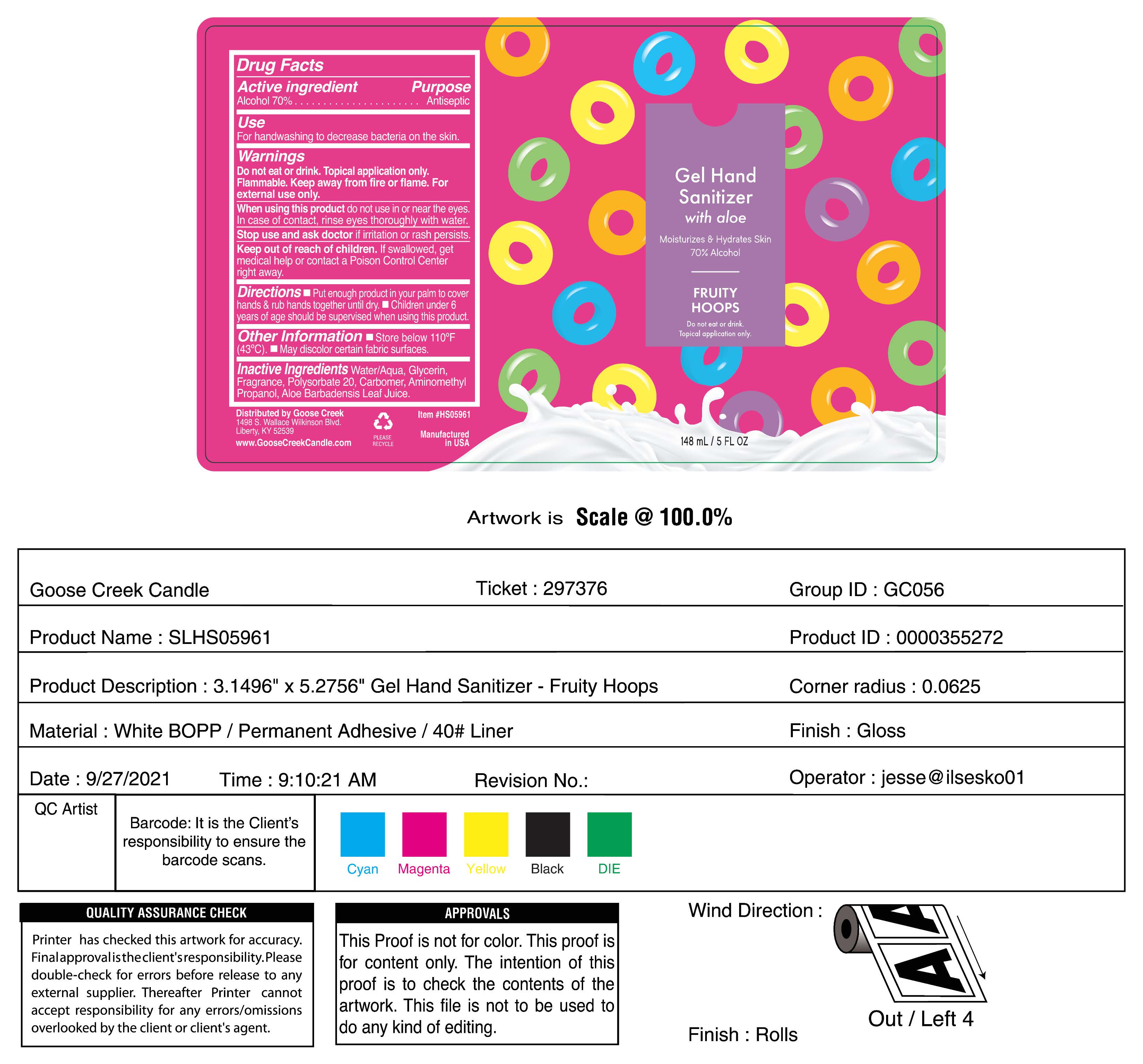 DRUG LABEL: Hand Sanitizer
NDC: 61354-027 | Form: LIQUID
Manufacturer: Oxygen Development LLC
Category: otc | Type: HUMAN OTC DRUG LABEL
Date: 20230210

ACTIVE INGREDIENTS: ALCOHOL 73.4 mL/100 mL
INACTIVE INGREDIENTS: GLYCERIN 1.49 mL/100 mL; CARBOMER HOMOPOLYMER, UNSPECIFIED TYPE 0.49 mL/100 mL; WATER 22.5 mL/100 mL; FRAGRANCE 13576 1 mL/100 mL; POLYSORBATE 20 0.98 mL/100 mL

Gel Hand Sanitizer with aloe. Moisturizes & hydrates Skin 70% Alcohol. Fruity Hoops.

Active ingredient

Alcohol 70%

Purpose

Antiseptic

Use

For handwashing to decrease bacteria on the skin.

Warnings

Do not eat or drink. Topical application only. Flammable. Keep away from fire or flame. For external use only.

When using this product do not use in or near the eyes. in case of contact, rinse eyes troroughly with water.

Stop use and ask doctor if irritation or rash persists.

Keep out of reach of children

If swallowed, get medical help or contact a poison Control Center right away

Directions

Put enough product in your palm to cover hands & rub hands together until dry. Children under 6 years of age should be supervised when using this product

Other Information

store below 110 F (43 C). May discolor certain fabric surfaces.

Inactive Ingredients

Water/Aqua, Glycerin, Fragrance, Polysorbate 20, Carbomer, Aminomethyl Propanol, Aloe Barbadensis Leaf Juice